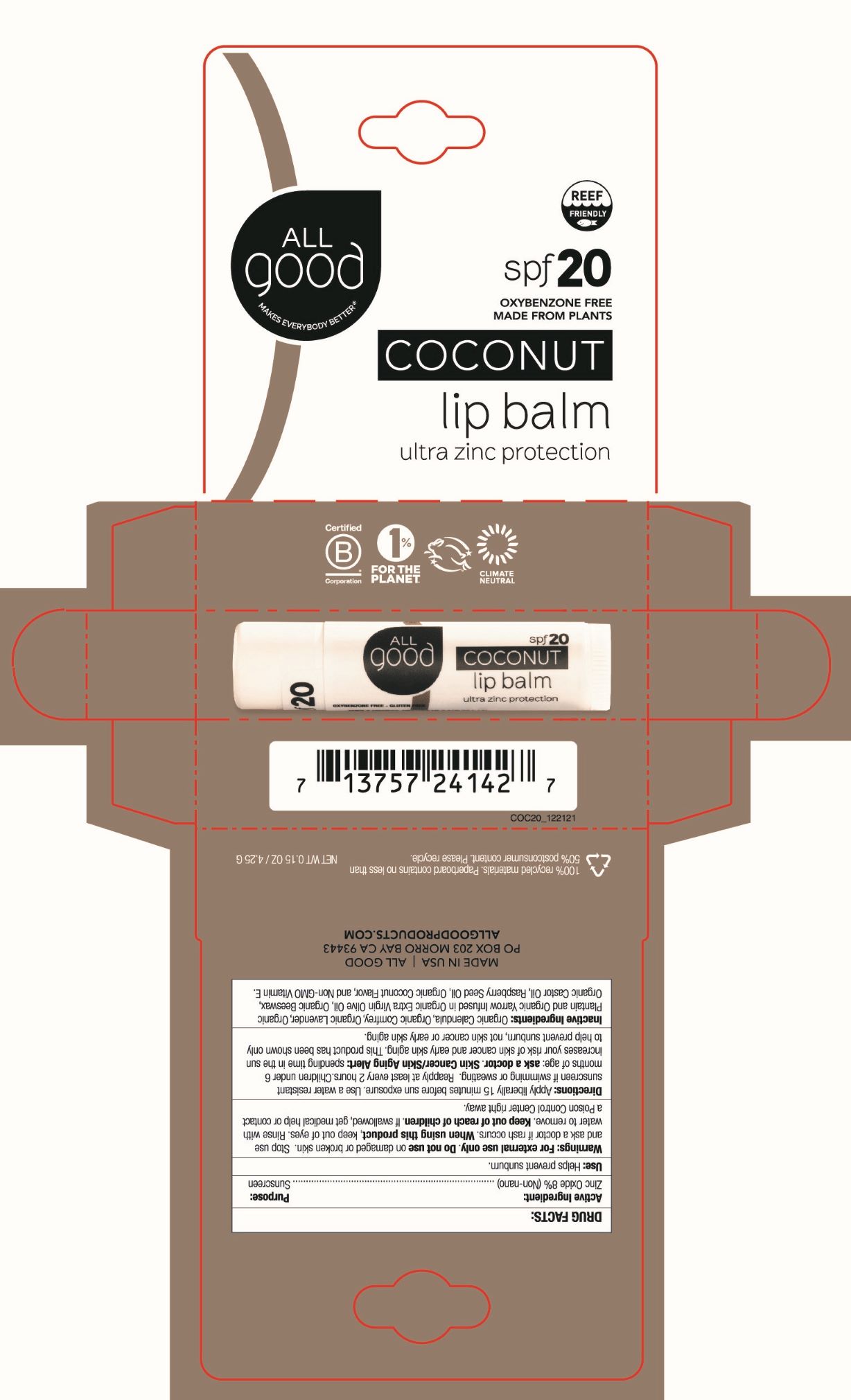 DRUG LABEL: All Good Coconut SPF 20 Zinc Oxide Lip Balm
NDC: 75786-224 | Form: STICK
Manufacturer: Elemental Herbs, Inc.
Category: otc | Type: HUMAN OTC DRUG LABEL
Date: 20240702

ACTIVE INGREDIENTS: ZINC OXIDE 8 g/100 g
INACTIVE INGREDIENTS: RASPBERRY SEED OIL; TOCOPHEROL; CALENDULA OFFICINALIS FLOWER; COMFREY LEAF; LAVENDER OIL; MUSA X PARADISIACA LEAF; CASTOR OIL; ACHILLEA MILLEFOLIUM ROOT OIL; YELLOW WAX; OLIVE OIL

All Good SPF 20 Coconut LipBalm

Drug Facts:

Active Ingredient:

Zinc Oxide 8% (Non-nano)

Purpose:

Sunscreen

INDICATIONS AND USAGE

Use: Helps prevent sunburn.

Warnings: For external use only

Do not use on damaged or broken skin.

Stop use and ask a doctor if rash occurs.

When using this product, keep out of eyes. Rinse with water to remove.

Keep out of reach of children. If swallowed, get medical help or contact a Poison Control Center right away.

DOSAGE AND ADMINISTRATION

Directions: Apply liberally 15 minutes before sun exposure. Use a water resistant sunscreen if swimming or sweating. Reapply at least every 2 hours. Children under 6 months of age: ask a doctor.

OTHER SAFETY INFORMATION

Skin Cancer/Skin Aging Alert: spending time in the sun increases your risk of skin cancer and early skin aging. This product has been shown only to help prevent sunburn, not skin cancer or early skin aging.

INACTIVE INGREDIENT

Inactive Ingredients: Organic Calendula, Organic Comfrey, Organic Lavender, Organic Plantain and Organic Yarrow Infused in Organic Extra Virgin Olive Oil, Organic Beeswax, Organic Castor Oil, Raspberry Seed Oil, Organic Coconut Flavor, and Non-GMO Vitamin E.

All Good SPF 20 Coconut Lip Balm

NET WT 0.15 OZ / 4.25 G

Oxybenzone-free

Made from Plants

ultra zinc protection

MADE IN USA

ALL GOOD

PO BOX 203 MORRO BAY CA 93443

ALLGOODPRODUCTS.COM